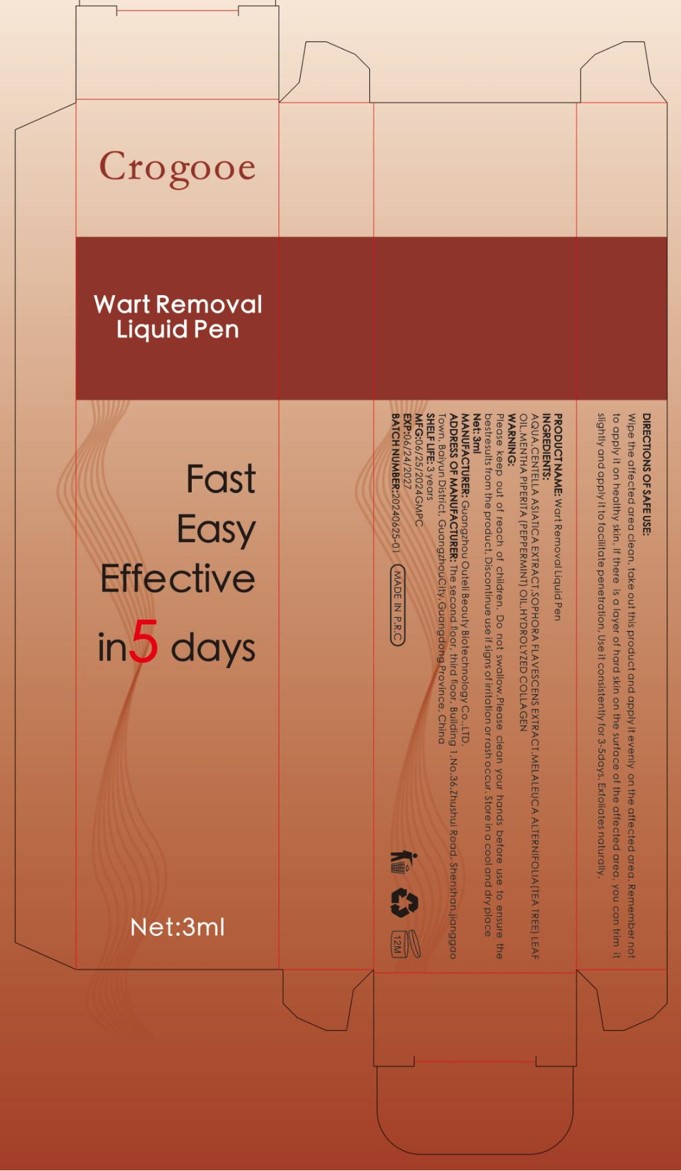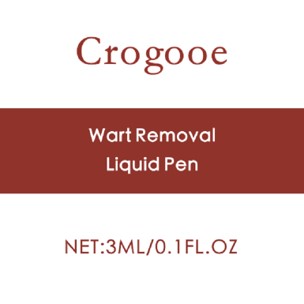 DRUG LABEL: Wart Removal Liquid Pen
NDC: 84458-001 | Form: LIQUID
Manufacturer: Dongguan LeTaoHui CrossBorder Ecommerce Co.
Category: otc | Type: HUMAN OTC DRUG LABEL
Date: 20240528

ACTIVE INGREDIENTS: MELALEUCA ALTERNIFOLIA LEAF 0.5 g/100 mL; CENTELLA ASIATICA TRITERPENOIDS 0.18 g/100 mL; STYPHNOLOBIUM JAPONICUM FLOWER BUD 0.5 g/100 mL; PEPPERMINT OIL 3 g/100 mL; HYDROLYSED BOVINE COLLAGEN (ENZYMATIC; 2000-5000 MW) 5 g/100 mL
INACTIVE INGREDIENTS: WATER

Wart Removal Liquid Pen

ACTIVE INGREDIENT

CENTELLA ASIATICA EXTRACT
SOPHORA FLAVESCENS EXTRACT
TEA TREEOIL
PEPPERMINT OIL
HYDROLYZED COLLAGEN

PURPOSE

Wart Removal
Liquid Pen

KEEP OUT OF REACH OF CHILDREN SECTION

INDICATIONS AND USAGE

Removing warts

WARNINGS

Please keep out of reach of children.
Do not swallow,Please clean your hands before use to ensure the bestresults from the product, Discontinue use if signs of iritatlon or rash occur. Store in a cool and dry place

DOSAGE AND ADMINISTRATION

Wipe the aflected area clean, take out this product and applyit evenly on the aflected area, Remember notto opply it on healthy skin, lf there is a layer of hard skin on the surfoce of the affected area, you can trim itslightly and apply it to facilitate penetration, Use it consistently for 3-5days.Exloliates naturally.

STORAGE AND HANDLING

Store in a cool and dry place.

SHELF LIFE: 3 years

INACTIVE INGREDIENT

WATER